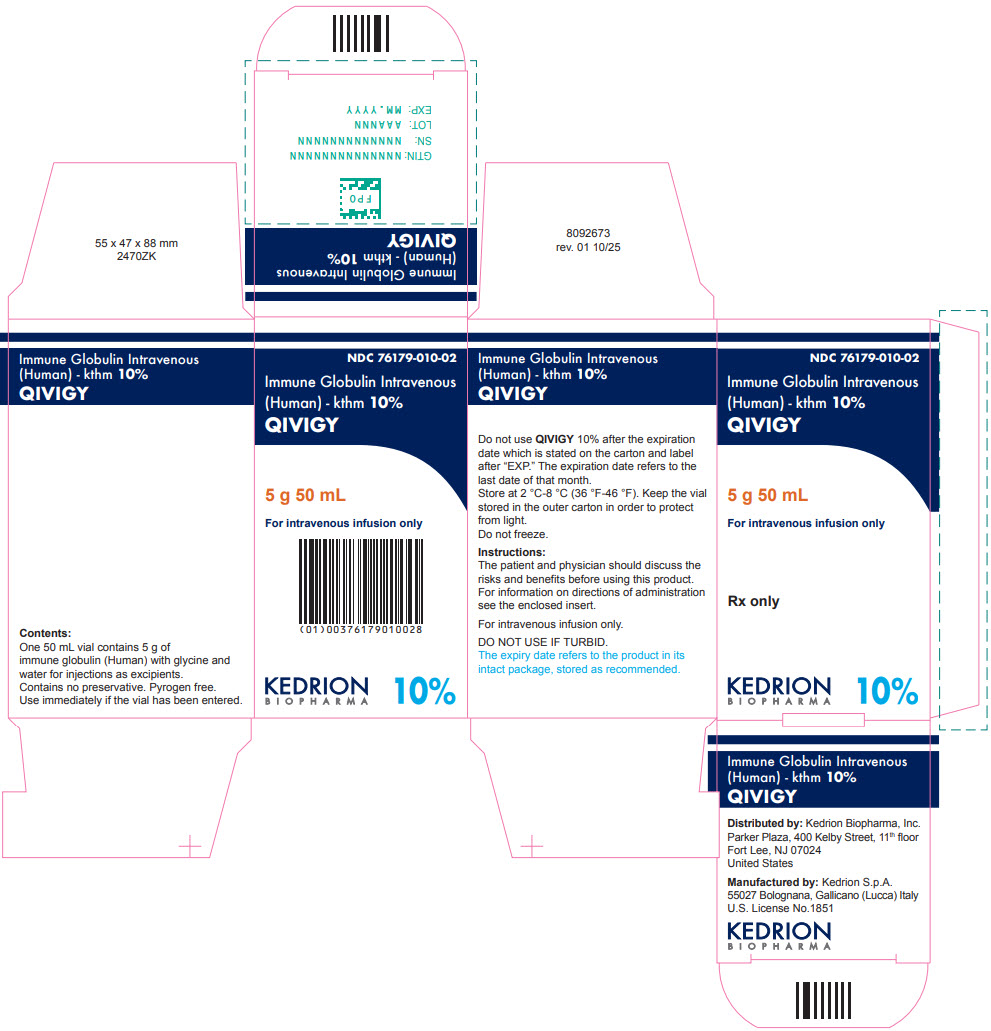 DRUG LABEL: QIVIGY 
NDC: 76179-010 | Form: INJECTION, SOLUTION
Manufacturer: Kedrion S.p.A.
Category: prescription | Type: HUMAN PRESCRIPTION DRUG LABEL
Date: 20251201

ACTIVE INGREDIENTS: human immunoglobulin g 5 mg/50 mL

HIGHLIGHTS OF PRESCRIBING INFORMATION

These highlights do not include all the information needed to use QIVIGY safely and effectively. See full prescribing information for QIVIGY.
QIVIGY (immune globulin intravenous, human-kthm) 10% solution
Initial U.S. Approval: 2025

WARNING: THROMBOSIS, RENAL DYSFUNCTION, AND ACUTE RENAL FAILURE

See full prescribing information for complete boxed warning.

- Thrombosis may occur with immune globulin products, including QIVIGY. Risk factors may include advanced age, prolonged immobilization, hypercoagulable conditions, history of venous or arterial thrombosis, use of estrogens, indwelling vascular catheters, hyperviscosity, and cardiovascular risk factors. (5.2)
- Renal dysfunction, acute renal failure, osmotic nephrosis may occur in predisposed patients with immune globulin intravenous (IGIV) products, including QIVIGY. Such events require immediate medical intervention; if not recognized or managed appropriately, may result in persistent or significant disability or incapacity or lead to fatal outcome. (5.3)
- For patients at risk of thrombosis, renal dysfunction or acute renal failure, administer QIVIGY at the minimum dose and infusion rate practicable. Ensure adequate hydration in patients before administration. Monitor for signs and symptoms of thrombosis and assess blood viscosity in patients at risk for hyperviscosity. (5.2, 5.3)

1 INDICATIONS AND USAGE

QIVIGY (immune globulin intravenous, human-kthm) 10% solution is indicated for treatment of adults with primary humoral immunodeficiency (PI). (1)

2 DOSAGE AND ADMINISTRATION

Intravenous Administration Only.

Dose | Infusion number | Initial Infusion Rate | Maintenance Infusion Rate (as tolerated)
300 - 800 mg/kg every 3-4 weeks | For the 1st infusion | 1 mg/kg/min (0.01 mL/kg/min) for 30 minutes | Increase every 30 minutes to a maximum of 8 mg/kg/min (0.08 mL/kg/min)
300 - 800 mg/kg every 3-4 weeks | From the 2nd infusion | 2 mg/kg/min (0.02 mL/kg/min) for 15 minutes | Increase every 15 minutes to a maximum of 8 mg/kg/min (0.08 mL/kg/min)

3 DOSAGE FORMS AND STRENGTHS

QIVIGY is a sterile, liquid solution 10% containing 100 mg/mL, in the following presentation:

- 5 g Immune Globulin per 50 mL single dose vial. (3)
- 10 g Immune Globulin per 100 mL single dose vial. (3)

4 CONTRAINDICATIONS

- Patients with history of anaphylactic or severe systemic reactions to human immune globulins. (4)
- IgA deficient patients with antibodies against IgA and a history of hypersensitivity. (4)

5 WARNINGS AND PRECAUTIONS

- Hypersensitivity Reactions: In case of a severe hypersensitivity reaction, discontinue QIVIGY infusion, and manage as appropriate. IgA deficient patients with antibodies against IgA are at greater risk of developing severe hypersensitivity and anaphylactic reactions. (5.1)
- Thrombotic events: Monitor patients with known risk factors for thrombotic events; consider baseline assessment of blood viscosity for patients at risk of hyperviscosity. (5.2)
- Hyperproteinemia, hyperviscosity, hyponatremia, or pseudohyponatremia may occur in patients receiving IGIV therapy. (5.4)
- Renal Injury: Ensure patients are not volume depleted before administering QIVIGY. Monitor renal function, including blood urea nitrogen, serum creatinine, and urine output in patients receiving QIVIGY prior to initial infusion and at appropriate intervals thereafter. (5.3)
- Aseptic Meningitis Syndrome (AMS) may occur, more frequently in association with high doses of IGIV or rapid infusion. (5.5)
- Hemolysis: Risk factors include high doses and non-O blood group. Monitor patients for hemolysis and hemolytic anemia. (5.6)
- Transfusion-related acute lung injury (TRALI): Monitor patients for symptoms of TRALI and manage using oxygen therapy with adequate ventilatory support as appropriate. (5.7)
- Transmission of infectious agents: QIVIGY is made from human plasma and may carry a risk of transmitting infectious agents. (5.8)

6 ADVERSE REACTIONS

The most common adverse reactions observed in ≥ 5% of patients were headache, fatigue, nausea, infusion-related reaction, Coombs direct test positive, sinusitis, dizziness and diarrhea. (6)

To report SUSPECTED ADVERSE REACTIONS, contact Kedrion Biopharma Inc. at 1-855-3KDRION (1-855-353-7466) or the FDA at 1-800-FDA-1088 or www.fda.gov/medwatch

7 DRUG INTERACTION

The passive transfer of antibodies may:

- Interfere with the response to live virus vaccines, such as measles, rubella, mumps and varicella. (7)
- Result in misleading positive results in serological testing. (5.9, 7)

8 USE IN SPECIFIC POPULATIONS

Geriatric: In patients over 65 years of age do not exceed the recommended dose and infuse QIVIGY at the minimum infusion rate practicable. (8.5)

FULL PRESCRIBING INFORMATION

WARNING: THROMBOSIS, RENAL DYSFUNCTION, AND ACUTE RENAL FAILURE

- Thrombosis may occur with immune globulin products, including QIVIGY. Risk factors may include: advanced age, prolonged immobilization, hypercoagulable conditions, history of venous or arterial thrombosis, use of estrogens, indwelling central vascular catheters, hyperviscosity, and cardiovascular risk factors. Thrombosis may occur in the absence of known risk factors [see Warnings and Precautions (5.2)].
- Renal dysfunction, acute renal failure, osmotic nephrosis may occur with immune globulin intravenous (IGIV) products in predisposed patients. Such events require immediate medical intervention, if not recognized or managed appropriately, may result in persistent or significant disability or incapacity or lead to fatal outcome. Patients predisposed to renal dysfunction include those with any degree of pre-existing renal insufficiency, diabetes mellitus, age greater than 65, volume depletion, sepsis, paraproteinemia, or patients receiving known nephrotoxic drugs [see Warnings and Precautions (5.3)].
- For patients at risk of thrombosis, renal dysfunction or failure, administer QIVIGY at the minimum dose available and the minimum infusion rate practicable. Ensure adequate hydration in patients before administration. Monitor for signs and symptoms of thrombosis and assess blood viscosity in patients at risk for hyperviscosity [see Warnings and Precautions (5.2, 5.3)].

1 INDICATIONS AND USAGE

QIVIGY (immune globulin intravenous, human-kthm) 10% solution is indicated for the treatment of adults with Primary Humoral Immunodeficiency (PI).

This includes, but is not limited to, congenital agammaglobulinemia, common variable immunodeficiency (CVID), X-linked agammaglobulinemia, Wiskott-Aldrich syndrome, and severe combined immunodeficiencies.

2 DOSAGE AND ADMINISTRATION

2.1 Recommended Dosage

Table 1. Recommended Dosage for QIVIGY
Dose | Infusion number | Initial Infusion Rate | Maintenance Infusion Rate (as tolerated)
300 - 800 mg/kg every 3-4 weeks | For the 1st infusion | 1 mg/kg/min (0.01 mL/kg/min) for 30 minutes | Increase every 30 minutes to a maximum of 8 mg/kg/min (0.08 mL/kg/min)
300 - 800 mg/kg every 3-4 weeks | From the 2nd infusion | 2 mg/kg/min (0.02 mL/kg/min) for 15 minutes | Increase every 15 minutes to a maximum of 8 mg/kg/min (0.08 mL/kg/min)

- Adjust frequency and dosage overtime to achieve target serum IgG levels and clinical response.
- If a patient misses a dose, administer the missed dose as soon as possible, and then resume scheduled treatments every 3 or 4 weeks, as applicable.
- In patients judged to have a potential increased risk for developing acute renal failure or thrombosis, QIVIGY should be administered at the minimum rate of infusion and dose practicable. In case of renal impairment, IGIV discontinuation should be considered [see Administration and Warnings and Precautions (2.3, 5.3)].

Measles pre-/post exposure prophylaxis

Post-exposure prophylaxis

If a patient has been exposed to measles, a dose of 400 mg/kg (4 mL/kg) of QIVIGY should be administered as soon as possible after exposure.

Pre-exposure prophylaxis

If a patient routinely receives a dose of less than 400 mg/kg of QIVIGY every 3 to 4 weeks (less than 4 mL/kg) and is at risk of measles exposure (i.e. traveling to a measles endemic area), administer a dose of at least 400 mg/kg (4 mL/kg) just prior to the expected measles exposure.

2.2 Preparation and Handling

- QIVIGY is a clear or slightly opalescent and colorless or pale-yellow solution. Inspect QIVIGY visually for particulate matter and discoloration prior to administration, whenever the solution and container permit. Do not use if the solution is cloudy, turbid, or if it contains particulate matter or deposits.
- Do not shake.
- Do not dilute.
- QIVIGY should be brought to room temperature before use (up to 25 °C [77 °F]).
- Keep the vial in the outer carton.
- If the packaging shows any signs of tampering, do not use the product and notify Kedrion Biopharma Inc. immediately at 1-855-3KDRION (1-855-353-7466).
- The QIVIGY vial is for single use only. Any vial that has been opened must be used immediately. QIVIGY contains no preservative.
- For administration of large doses, pool multiple vials using aseptic technique
- Infuse QIVIGY using a separate infusion line. At the end of the infusion flush tubing with saline solution or Dextrose 5% in water (D5W) to ensure that the entire dose is administered.
- Do not mix QIVIGY with other IGIV products or other intravenous medications (including normal saline)
- Do not use after expiration date.
- Record the batch number every time QIVIGY is administered to a patient.
- Dispose partially used or unused product or waste material in accordance with local requirements.

2.3 Administration

Intravenous administration only.

- Hydrate the patient adequately prior to the initiation of infusion.
- Infuse QIVIGY intravenously using an intravenous infusion set. See Table 1 for recommended infusion rates.
- Monitor patient vital signs throughout the infusion.
- The rate of infusion can be related to certain severe adverse drug reactions. Slow or stop infusion if adverse reactions occur.
- If symptoms subside promptly, resume infusion at a lower rate as tolerated by the patient.
- The observation time of patients after QIVIGY administration may vary. If the patient (a) has not received QIVIGY or another IgG product, (b) is switched from an alternative IGIV product or (c) has had a long interval since the previous infusion, prolong the observation time for adverse reactions after QIVIGY infusion.
- Ensure that patients with pre-existing renal insufficiency are not volume depleted. For patients at risk of renal dysfunction or thrombosis, administer QIVIGY at the minimum dose and infusion rate practicable and discontinue QIVIGY if renal function deteriorates [see Boxed Warning, Warnings and Precautions (5.2, 5.3)].

3 DOSAGE FORMS AND STRENGTHS

QIVIGY is a liquid, sterile solution for infusion 10% IgG (100 mg/mL), for intravenous infusion in the following presentation:

- 5 g Immune Globulin per 50 mL single dose vial
- 10 g Immune Globulin per 100 mL single dose vial

4 CONTRAINDICATIONS

QIVIGY is contraindicated in patients who have had an anaphylactic or severe systemic reaction to the administration of human immune globulin.

QIVIGY is contraindicated in IgA deficient patients with antibodies against IgA and history of hypersensitivity [see Warnings and Precautions (5.1)].

5 WARNINGS AND PRECAUTIONS

5.1 Hypersensitivity

Severe hypersensitivity reactions, including anaphylaxis, may occur with QIVIGY [see Adverse Reactions (6)] In case of hypersensitivity, discontinue QIVIGY infusion immediately and institute appropriate treatment. Medications such as epinephrine should be available for immediate treatment of acute hypersensitivity reactions.

QIVIGY contains IgA (≤ 50 mg/L) [see Description (11)]. Patients with known antibodies to IgA may have a greater risk of developing potentially severe hypersensitivity and anaphylactic reactions. QIVIGY is contraindicated in IgA deficient patients with antibodies against IgA and patients with a history of hypersensitivity reaction [see Contraindications (4)].

5.2 Thrombosis

Thrombosis may occur following treatment with immune globulin products, including QIVIGY. Risk factors may include advanced age, prolonged immobilization, hypercoagulable conditions, history of venous or arterial thrombosis, use of estrogens, indwelling central vascular catheters, hyperviscosity, and cardiovascular risk factors. Thrombosis may occur in the absence of known risk factors.

Consider baseline assessment of blood viscosity in patients at risk for hyperviscosity, including those with cryoglobulins, fasting chylomicronemia, high triacylglycerols (triglycerides), or monoclonal gammopathies. For patients at risk of thrombosis, administer QIVIGY at the minimum dose and infusion rate practicable. Ensure adequate hydration in patients before administration. Monitor for signs and symptoms of thrombosis [see Boxed Warning, Dosage and Administration (2)].

5.3 Renal Injury

Renal injury including acute renal dysfunction, acute renal failure, acute tubular necrosis, proximal tubular nephropathy, and, osmotic nephrosis may occur after treatment with immune globulin products including QIVIGY. Ensure that patients are not volume depleted prior to the initiation of the infusion of QIVIGY. For patients judged to be at risk for developing renal dysfunction because of pre-existing renal insufficiency or predisposition to acute renal failure (such as diabetes mellitus, hypovolemia, overweight, use of concomitant nephrotoxic drugs, or age over 65 years), administer QIVIGY at the minimum infusion rate practicable [see Dosage and Administration (2)]. The risk of renal dysfunction and acute renal failure is greater in products that contain sucrose, though may still occur in products without sucrose. QIVIGY does not contain sucrose.

Conduct periodic monitoring of renal function and urine output in patients judged to be at increased risk of developing acute renal failure. Assess renal function, including measurement of blood urea nitrogen (BUN) and serum creatinine, before the initial infusion of QIVIGY and at appropriate intervals thereafter. If renal function deteriorates, consider discontinuing QIVIGY [see Dosage and Administration (2)].

5.4 Hyperproteinemia, Increased Serum Viscosity, and Hyponatremia

Hyperproteinemia, hyperviscosity, and hyponatremia may occur in patients receiving immune globulin treatment, including QIVIGY. It is critical to clinically distinguish true hyponatremia from a pseudohyponatremia that is associated with or causally related to hyperproteinemia with concomitant decreased calculated serum osmolality or elevated osmolar gap, because treatment aimed at decreasing serum free water in patients with pseudohyponatremia may lead to volume depletion, a further increase in serum viscosity and a possible predisposition to thromboembolic events.

5.5 Aseptic Meningitis Syndrome

Aseptic meningitis syndrome (AMS) may occur in patients following immune globulin treatment, including QIVIGY. The risk of AMS may be higher with high doses (2 g/kg) and/or rapid infusion of immune globulin products. AMS usually begins within several hours to two days following immune globulin treatment and is characterized by the following symptoms and signs: severe headache, nuchal rigidity, drowsiness, fever, photophobia, painful eye movements, nausea and vomiting. Cerebrospinal fluid (CSF) studies frequently reveal pleocytosis up to several thousand cells per cubic millimeter, predominantly from the granulocytic series, and elevated protein levels up to several hundred mg/dL, but negative culture results. Conduct a thorough neurological examination on patients exhibiting symptoms and signs of AMS, including CSF studies, to rule out other causes of meningitis. Discontinuation of immune globulin treatment has resulted in remission of AMS within several days without sequelae.

5.6 Hemolysis

Hemolysis may occur after administration of immune globulin products, including QIVIGY due to the presence of blood group antibodies that can act as hemolysins and induce in vivo coating of red blood cells (RBCs) with immune globulin, causing a positive direct antiglobulin test and hemolysis. Delayed hemolytic anemia can develop after immune globulin treatment due to enhanced RBC sequestration, and acute hemolysis consistent with intravascular hemolysis has been reported.

The risk factors for hemolysis include high doses (e.g., ≥ 2 g/kg) given either as a single administration or divided over several days, non-O blood group, and an underlying inflammatory disease condition.

Monitor patients for clinical signs and symptoms of hemolysis. Consider appropriate laboratory testing in higher risk patients, including measurement of hemoglobin or hematocrit prior to infusion and within approximately 36 hours and again 7 to 10 days post infusion. If clinical signs and symptoms of hemolysis or a significant drop in hemoglobin or hematocrit are observed after QIVIGY infusion, perform confirmatory laboratory testing.

5.7 Transfusion-related Acute Lung Injury

Transfusion-Related Acute Lung Injury (TRALI) may occur in patients following immune globulin treatment, including QIVIGY. TRALI is characterized by severe respiratory distress, pulmonary edema, hypoxemia, normal left ventricular function, and fever. Symptoms typically appear within 1 to 6 hours after treatment.

Monitor patients for pulmonary adverse reactions. If TRALI is suspected, immediately stop QIVIGY infusion, and perform appropriate tests for the presence of anti-neutrophil antibodies and anti-human leukocyte antigen (HLA) antibodies in both the product and patient's serum. Manage patients using oxygen therapy with adequate ventilatory support as appropriate.

5.8 Transmissible Infectious Agents

There is risk of transmission of infectious disease or agents including viruses, the variant Creutzfeldt-Jakob disease (vCJD) agent, and the Creutzfeldt-Jakob disease agent with QIVIGY administration because it is manufactured using human blood. The risk of infectious agent transmission is minimized by plasma donor screening, donation testing, and manufacturing steps proven to inactivate and remove bloodborne pathogens.

Any infection suspected to have been transmitted by this product should be reported by the physician or other healthcare provider to Kedrion Biopharma Inc. at 1-855-3KDRION (1-855-353-7466).

5.9 Monitoring Laboratory Tests

- Assess renal function, including measurement of BUN and serum creatinine, before the initial infusion of QIVIGY and at appropriate intervals thereafter [see Warnings and Precautions (5.3)].
- Consider baseline assessment of blood viscosity in patients at risk for hyperviscosity, including those with cryoglobulins, fasting chylomicronemia, markedly high triacylglycerols (triglycerides), or monoclonal gammopathies, because of the potentially increased risk of thrombosis [see Warnings and Precautions (5.2)].
- If signs and/or symptoms of hemolysis are present after an infusion of QIVIGY, perform appropriate laboratory testing for confirmation [see Warnings and Precautions (5.6)].
- If TRALI is suspected, perform appropriate tests for the presence of anti-neutrophil antibodies and anti-HLA antibodies in both the product and the patient's serum [see Warnings and Precautions (5.7)].

5.10 Interference with Laboratory Tests

After the administration of immune globulin, the transitory rise of the various passively transferred antibodies in the patients' blood may result in misleading positive results in serological testing. Passive transmission of antibodies to erythrocyte antigens, e.g. A, B, D may interfere with some serological tests for red cell antibodies for example the direct or indirect antiglobulin test (Coombs test).

6 ADVERSE REACTIONS

6.1 Clinical Trials Experience

Because clinical studies are conducted under widely varying conditions, adverse reaction rates observed in the clinical trials of one drug cannot be directly compared to rates in other clinical trials of another drug and may not reflect the rates observed in clinical practice.

The safety data described in this section reflects exposure to QIVIGY in one clinical study. A total of 47 patients with PI received intravenous infusion of QIVIGY at a dose range of 266 to 826 mg/kg every 3 or 4 weeks for up to 12 months [see Clinical Studies (14)]. A total of 643 infusions of QIVIGY were administered, 136 in the every 3-week schedule and 507 in the 4-week schedule. During the study, 4 out of 47 (9%) patients received premedication.

The most common product-related adverse events observed in ≥ 5% of clinical study patients with PI were headache, infusion-related reaction, Coombs direct test positive, fatigue, and nausea. Table 2 lists the most common adverse reactions reported in ≥5% of patients.

Table 2: Adverse Reactions [Adverse reactions were defined as adverse events occurring during or within 72 hours of infusion or any causally related event occurring within the study period.] Occurring in ≥ 5% of Patients
Adverse Reaction | By Patients n (%) [n = 47] | By Infusions n (%) [n = 643]
Headache | 14 (30) | 26 (4)
Fatigue | 7 (15) | 10 (2)
Nausea | 6 (13) | 6 (<1)
Infusion-related Reaction | 5 (11) | 7 (1)
Coombs Direct Test Positive | 5 (11) | 8 (1)
Sinusitis | 3 (6) | 3 (<1)
Dizziness | 3 (6) | 3 (<1)
Diarrhea | 3 (6) | 4 (<1)

6.2 Postmarketing Experience

Because adverse reactions are reported voluntarily from a population of uncertain size, it is not always possible to reliably estimate their frequency or establish a causal relationship to drug exposure. The following adverse reactions have been identified and reported during the post-approval use of IGIV products:

- Respiratory: Apnea, Acute Respiratory Distress Syndrome (ARDS), Transfusion-Related Acute Lung Injury (TRALI), respiratory failure, hypoxemia, pulmonary edema, dyspnea, wheezing, cough, bronchospasm, pulmonary embolism.
- Cardiovascular: Cardiac arrest, thromboembolism, vascular collapse, hypotension, phlebitis, pallor, angina, tachycardia, bradycardia, palpitations, myocardial infarction, cyanosis.
- Neurological: Coma, loss of consciousness, seizures, (acute) encephalopathy, tremor, aseptic meningitis syndrome, migraine, speech disorder, paresthesia, hypoesthesia, photophobia.
- Integumentary: Stevens-Johnson syndrome, epidermolysis, erythema multiforme, bullous dermatitis, eczema, erythematous rash, dermatitis, pruritus, alopecia, urticaria.
- Gastrointestinal: Hepatic dysfunction, abdominal pain, diarrhea.
- Renal: Acute renal failure, osmotic nephropathy, renal pain.
- Hematologic: Pancytopenia, leukopenia, hemolysis.
- Musculoskeletal: Musculoskeletal pain, muscle spasm, arthralgia, myalgia, muscle stiffness.
- General disorders and administration site conditions: Pyrexia, rigors, injection-site reactions, chills, flushing, lethargy, malaise, burning sensation.
- Psychiatric disorders: Confusion, anxiety, agitation, nervousness.
- Metabolic and nutritional: Fluid overload, (pseudo) hyponatremia.
- Immune system disorders: Hypersensitivity (e.g. anaphylaxis, allergic reaction), angioedema.
- Investigations: Falsely elevated erythrocyte sedimentation rate, positive direct antiglobulin (Coombs') test, increased hepatic enzymes.

7 DRUG INTERACTION

7.1 Effect of QIVIGY on Live attenuated virus vaccines

Immune globulin administration may transiently impair the efficacy of live attenuated virus vaccines such as measles, mumps, rubella, s and varicella because the continued presence of high levels of passively acquired antibody may interfere with an active antibody response. Inform the immunizing physician of recent therapy with QIVIGY so that appropriate measures may be taken.

7.2 Effect of QIVIGY on Serological Testing

Passive transmission of antibodies through immune globulin administration may interfere with some serological testing [see Warnings and Precautions (5.10)].

7.3 Effect of Loop diuretics on QIVIGY

The use of loop diuretics should be avoided. Concomitant use of loop diuretics with IGIV may contribute to an increased blood viscosity and subsequently increase the risk of thromboembolic events.

8 USE IN SPECIFIC POPULATIONS

8.1 Pregnancy

Risk Summary

No human data are available to indicate the presence or absence of drug-associated risk. Animal reproduction studies have not been conducted with QIVIGY. It is not known whether QIVIGY can cause fetal harm when administered to a pregnant woman or can affect reproduction capacity. Immune globulins cross the placenta from maternal circulation. QIVIGY should be given to pregnant women only if clearly needed. In the U.S. general population, the estimated background risk of major birth defect and miscarriage in clinically recognized pregnancies is 2 - 4% and 15 - 20%, respectively.

8.2 Lactation

Risk Summary

No human data are available to indicate the presence or absence of drug-associated risk. Immune globulins are excreted in human milk. The developmental and health benefits of breastfeeding should be considered along with the mother's clinical need for QIVIGY and any potential adverse effects on the breastfed infant from QIVIGY or from the underlying maternal condition.

8.4 Pediatric Use

The safety and effectiveness of QIVIGY have not been established in pediatric patients.

8.5 Geriatric Use

Seven patients with PI at or over the age of 65 years were included in the clinical study of QIVIGY. Clinical study of QIVIGY did not include sufficient numbers of patients aged 65 and over to determine whether they respond differently than younger patients.

Use caution when administering QIVIGY to patients aged 65 and over who are at increased risk for renal insufficiency or thrombosis [see Boxed Warning, Warnings and Precautions (5.2, 5.3)]. For geriatric patients at risk of thrombosis or acute renal failure, administer QIVIGY at the minimum dose and infusion rate practicable.

10 OVERDOSAGE

Overdosage of QIVIGY may lead to fluid overload and hyperviscosity, particularly in the elderly and in patients with renal impairment.

11 DESCRIPTION

QIVIGY (immune globulin intravenous, human-kthm) is a ready-to-use, sterile, non-pyrogenic liquid solution of human immune globulin (IgG) for intravenous administration. QIVIGY is clear or slightly opalescent, colorless or pale yellow. QIVIGY consists of immune globulin of which IgG represents at least 96% of the total protein. It consists of 9 - 11% protein in 0.20 - 0.28 M glycine. In the solution, the IgG proteins are present by more than 97% (at lot release) and 93% (by expiration date) in monomeric and dimeric forms. Minimum value for osmolality is: 240 mOsmol/Kg. pH of the solution is in the range of 4.0 - 4.5. It contains trace levels of IgA (not more than 50 mg/L). The main component of QIVIGY is IgG (≥ 96%) with a sub-class distribution compatible with native human plasma. QIVIGY contains no carbohydrate stabilizers (e.g., sucrose, maltose) and no preservative.

To specifically reduce the anti-A and anti-B titers in the drug product (isoagglutinins A and B), donor plasma is screened for isoagglutinin titer using a validated assay, and plasma units with high agglutination scores are excluded from further processing. All donors of plasma are carefully screened by history and laboratory testing to reduce the risk of transmitting blood-borne pathogens from infected donors. All plasma units used in the manufacture of QIVIGY are tested and approved for manufacture using FDA-licensed serological assays for Hepatitis B surface antigen (HBsAg), Human immunodeficiency virus 1/2 antibodies (anti-HIV-1/2), and Hepatitis C antibodies (anti-HCV). In addition, donations are screened for Hepatitis C virus (HCV), Human immunodeficiency virus 1 (HIV-1), Hepatitis B virus (HBV), Hepatitis A virus (HAV) and Parvovirus B19 (B19V) by NAT. Further testing is performed on the manufacturing pools for HBsAg and antibodies to HIV-1/2; plasma pools are also tested for HCV, HIV-1, HBV, HAV and B19V by NAT with the limit for B19V set to not exceed 10^4 IU B19V DNA per mL plasma.

QIVIGY is made from large pools of human plasma by a combination of cold alcohol fractionation, caprylate precipitation and filtration, anion-exchange chromatography, nanofiltration and ultrafiltration/diafiltration (UF/DF). QIVIGY is incubated in the final container at the low pH of 4.0 – 4.5. The product is intended for intravenous administration.

The capacity of the manufacturing process to remove and/or inactivate enveloped and non-enveloped viruses has been validated by spiking studies at laboratory scale with a validated model of the manufacturing processes, using the following enveloped and non-enveloped viruses: HIV-1 as the relevant virus for HIV-1 and HIV–2; Bovine Viral Diarrhea virus (BVDV) as a model for HCV; Pseudorabies virus (PRV) as a model for large enveloped DNA viruses (e.g., Herpes viruses and HBV); HAV as relevant non-enveloped virus, Encephalomyocarditis virus (EMCV) as a model for HAV, and Porcine Parvovirus (PPV) as a model for human parvovirus B19.

The viral clearance capacity of QIVIGY manufacturing process has been evaluated by summing logarithmic reduction factors from single steps with significant reduction factors more than 1 log, obtaining overall log reduction factors (LRFs) reported in Table 3.

The manufacturing process for QIVIGY includes four steps to reduce the risk of virus transmission. Two of these are dedicated virus clearance steps: sodium caprylate incubation to inactivate enveloped viruses and virus filtration to remove, by size exclusion, both enveloped and non-enveloped viruses as small as approximately 20 nanometers. In addition, caprylate precipitation and filtration step and low pH treatment step contributes to the virus reduction capacity.

Overall virus reduction was calculated only from steps that were orthogonal in mechanisms of removal/inactivation. In addition, each step was verified to provide robust virus reduction across the production range for key operating parameters.

Table 3: Viral Inactivation/Removal Capacity of the QIVIGY Manufacturing
Process | LRF | Enveloped | Viruses | LRF | Non-Enveloped | Viruses
Step | BVDV | HIV-1 | PsRV | HAV | PPV | EMCV
1st Caprylate (precipitation+depth filtration) | 3.35 | NI | NI | > 5.93 | 2.69 | NI
2nd Caprylate (inactivation) | > 5.37 | > 4.54 | > 6.79 | NA | NA | NA
Nanofiltration | > 5.26 | 2.27 | NI [Due to the low pH condition at which nanofiltration was performed, PsRV was immediately inactivated and it was not possible to properly evaluate virus removal by nanofiltration.] | > 4.85 | > 6.19 | > 4.28
Inactivation by Low pH | 2.45 | 6.17 | 6.65 | NI | NI | 3.43
Overall Viral Reduction | > 16.43 | > 12.98 | > 13.44 | > 10.78 | > 8.88 | > 7.71
NI: not investigated.
NA: Not applicable.

Concerning vCJD risk, donor exclusion criteria are in accordance with the relevant FDA Guidance for Industry (Recommendations to Reduce the Possible Risk of Transmission of Creutzfeldt-Jakob Disease and Variant Creutzfeldt-Jakob Disease (vCJD) by Blood and Blood Components, current edition).

12 CLINICAL PHARMACOLOGY

12.1 Mechanism of Action

QIVIGY is an IgG replacement therapy for primary humoral immunodeficiency. QIVIGY supplies a broad spectrum of opsonizing and neutralizing IgG antibodies against bacterial and, viral agents. The mechanism of action of IgG in PI has not been fully elucidated.

12.2 Pharmacodynamics

QIVIGY contains mainly immunoglobulin G (IgG) with a broad spectrum of antibodies against various infectious agents reflecting the IgG activity found in the donor population. QIVIGY which is prepared from pooled material from not less than 1000 donors, has an IgG subclass distribution similar to that of native human plasma. Adequate doses of IGIV can restore abnormally low IgG level to the normal range. Standard pharmacodynamic studies were not performed.

12.3 Pharmacokinetics

In the clinical study assessing the efficacy and safety of QIVIGY in 47 patients with PI [see Clinical Studies (14)], serum concentrations of total IgG were measured in 23 patients following the 5th infusion of QIVIGY for patients on the 4-week dosing schedule, or the 7th infusion for patients on the 3-week dosing schedule. The dose of QIVIGY used in these patients ranged from 266 mg/kg to 826 mg/kg. After infusion, blood samples for PK analyses were collected until Day 21 or Day 28 for patients treated according to the 3-week and 4-week schedule, respectively. Table 4 summarizes the PK parameters of QIVIGY based on serum concentrations of total IgG.

Table 4: Pharmacokinetic Parameters of QIVIGY
Parameter | 3-Week Dosing Interval (n=5) | 4-Week Dosing Interval (n=18)
(unit) | Mean [Arithmetic mean] (CV%) | Mean (CV%)
Cmax (mg/dL) | 2680 (10.5) | 2300 (20.3)
Cmin (mg/dL) | 1140 (13.2) | 994 (20.2)
Tmax (h) [Median and range are presented for tmax.] | 0.53 (0.5 - 2.02) | 0.52 (0.5 - 23.8)
AUC(0-t) (day*mg/dL) | 31700 (19.0) | 37300 (20.7)
AUCtau (day*mg/dL) | 34000 (10.7) | 38000 (17.1)
Half-life (day) | 24.5 (9.92) | 37.3 (30.1)
Clearance (dL/day/kg) | 0.019 (15.8) | 0.014 (25.5)
Volume of distribution (dL/kg) | 0.67 (6.0) | 0.70 (16.9)
AUC(0-t) = area under the concentration-time curve from time 0 to the time t of the last quantifiable concentration, AUCtau = area under the concentration versus time curve within a dosing interval, tau = dosing interval, Cmax = maximum observed concentration, Tmax = time at which Cmax was apparent, CV% = coefficient of variation.

13 NONCLINICAL TOXICOLOGY

13.1 Carcinogenesis, mutagenesis, impairment of fertility

No animal studies were conducted to evaluate the carcinogenic or mutagenic effect of QIVIGY or its effects on fertility.

13.2 Animal toxicology and/or pharmacology

An acute animal toxicology study was conducted to evaluate possible toxicity of QIVIGY before clinical trial. There were no toxicological concerns for the therapeutic use of QIVIGY.

14 CLINICAL STUDIES

The efficacy of QIVIGY was evaluated in an open-label, prospective clinical study in adult patients with primary humoral immunodeficiency (NCT03961009). A total of 47 patients received intravenous infusion of QIVIGY at the dose of 266 to 826 mg/kg every 3 or 4 weeks for 12 months. Thirty-nine and 8 patients were administered QIVIGY on a 4-week or a 3-week infusion cycle, respectively.

The population characteristics were as follows: The median age was 56 years (range 20 to 70 years), 30 patients (64%) were female, 45 patients (96%) were White, and 2 patients (4%) were of "other" race.

The primary efficacy outcome was the incidence rate of acute serious bacterial infections (SBIs; bacterial pneumonia, bacteremia/sepsis, bacterial meningitis, visceral abscess, and osteomyelitis/septic arthritis). Secondary efficacy outcomes included the incidence rate of infections other than acute SBIs, patients hospitalized due to infection, number and duration of antibiotic treatment for any kind of infection, and missed work/school/other major activities due to infections. Table 5 summarizes the efficacy results.

Table 5: Summary of QIVIGY Efficacy Results (N=47)
Efficacy Outcome | Result
Annualized rate of acute SBIs | 0 acute SBIs/person-year
Annualized rate of other infections (not including acute SBIs) | 2.1 infections per patient year
Patients hospitalized due to infection | 0
Antibiotics
Number of antibiotics courses | 113
Median duration of antibiotic use (min, max) | 10 (1, 334) days
Missed work/school/other major activities due to infections
Number of patients | 9
Median (min, max) | 6 (1, 53) days

16 HOW SUPPLIED/STORAGE AND HANDLING

QIVIGY is supplied in single-dose, tamper evident vials containing the labeled amount of functionally active IgG. The vial labels incorporate integrated hangers. The components used in the packaging for QIVIGY are not made with natural rubber latex.

Each product presentation includes a package insert and the components are listed in Table 6.

Table 6: Package Insert and components of QIVIGY presentations
Presentation | NDC Number of Carton | NDC Number of Label
50 mL Vial containing 5 grams of protein | 76179-010-01 | 76179-010-02
100 mL Vial containing 10 grams of protein | 76179-010-03 | 76179-010-04

Storage

Do not use QIVIGY after the expiration date which is stated on the carton and label after "EXP." The expiration date refers to the last day of that month.

Store QIVIGY at 2 °C - 8 °C (36 °F - 46 °F) for up to 36 months.

Keep the vial stored in the outer carton in order to protect from light.

Do not freeze.

17 PATIENT COUNSELING INFORMATION

Discuss the following with the patient.

- Hypersensitivity Reactions: Inform patients that hypersensitivity reactions may occur with QIVIGY infusion. Prior to starting QIVIGY ask about a history of allergic reactions to immune globulin or other blood products. Advise patients to seek immediate medical evaluation if any signs and symptoms of hypersensitivity or acute infusion reactions occur [see Warnings and precautions (5.1)].
- Renal Injury: Inform patients that renal injury may occur with QIVIGY infusion. Advise patients to seek immediate medical evaluation if any signs and symptoms of renal injury occur such as decreased urine output, sudden weight gain, fluid retention/edema, and/or shortness of breath [see Warnings and Precautions (5.3)].
- Thrombosis: Inform patients that thrombosis may occur after QIVIGY infusion. Advise patients to seek immediate medical evaluation if any signs and symptoms of thrombosis occur such as pain and/or swelling of an arm or leg with warmth over the affected area, discoloration of an arm or leg, unexplained shortness of breath, chest pain or discomfort that worsens on deep breathing, unexplained rapid pulse, numbness or weakness on one side of the body [see Warnings and Precautions (5.2)]
- Aseptic meningitis syndrome (AMS): Inform patients that AMS may occur after QIVIGY infusion. Advise patients to seek immediate medical evaluation if any signs and symptoms of AMS occur such as severe headache, neck stiffness, drowsiness, fever, sensitivity to light, painful eye movements, nausea, and vomiting [see Warnings and Precautions (5.5)]
- Hemolysis: Inform patients that hemolysis may occur after QIVIGY infusion. Advise patients to seek immediate medical evaluation if any signs and symptoms of hemolysis occur such as fatigue, increased heart rate, yellowing of the skin or eyes, and dark-colored urine [see Warnings and Precautions (5.6)]
- Transfusion-Related Acute Lung Injury (TRALI): Inform patients that TRALI may occur after QIVIGY infusion. Advise patients to seek immediate medical evaluation if any signs and symptoms of TRALI occur such as breathing difficulty, chest pain, blue lips or extremities, and fever [see Warnings and Precautions (5.7)].
- Transmission of Infectious Agents: Inform patients that QIVIGY is a derivative of human plasma and may contain infectious agents that cause disease (e.g., viruses, vCJD agent and, theoretically, CJD agent). Inform patients that the risk that QIVIGY may transmit an infectious agent has been reduced by screening plasma donors for prior exposure for certain viruses, by testing the donated plasma for certain virus infections, and by inactivating and/or removing certain viruses during manufacturing [see Warnings and Precautions (5.8)].
- Drug Interactions: Inform patients that QIVIGY can interfere with their immune response to live virus vaccines such as measles, mumps, varicella and rubella. Inform patients to notify their healthcare professional of this potential interaction when they are receiving vaccinations [see Drug Interactions (7)].

Distributed by:
Kedrion Biopharma Inc.
Parker Plaza, 400 Kelby Street 11th floor
Fort Lee, NJ 07024
United States

Manufactured by:
Kedrion S.p.A.
Via Provinciale Loc. Bolognana
55027 Gallicano (Lucca)
Italy
Phone: +39 0583 1969 1
Fax: +39 0583 1969 981
U.S. License No. 1851

PRINCIPAL DISPLAY PANEL - 50 mL Vial Carton

NDC 76179-010-02

Immune Globulin Intravenous
(Human) - kthm 10%
QIVIGY

5 g 50 mL

For intravenous infusion only

Rx only

KEDRION
BIOPHARMA

10%